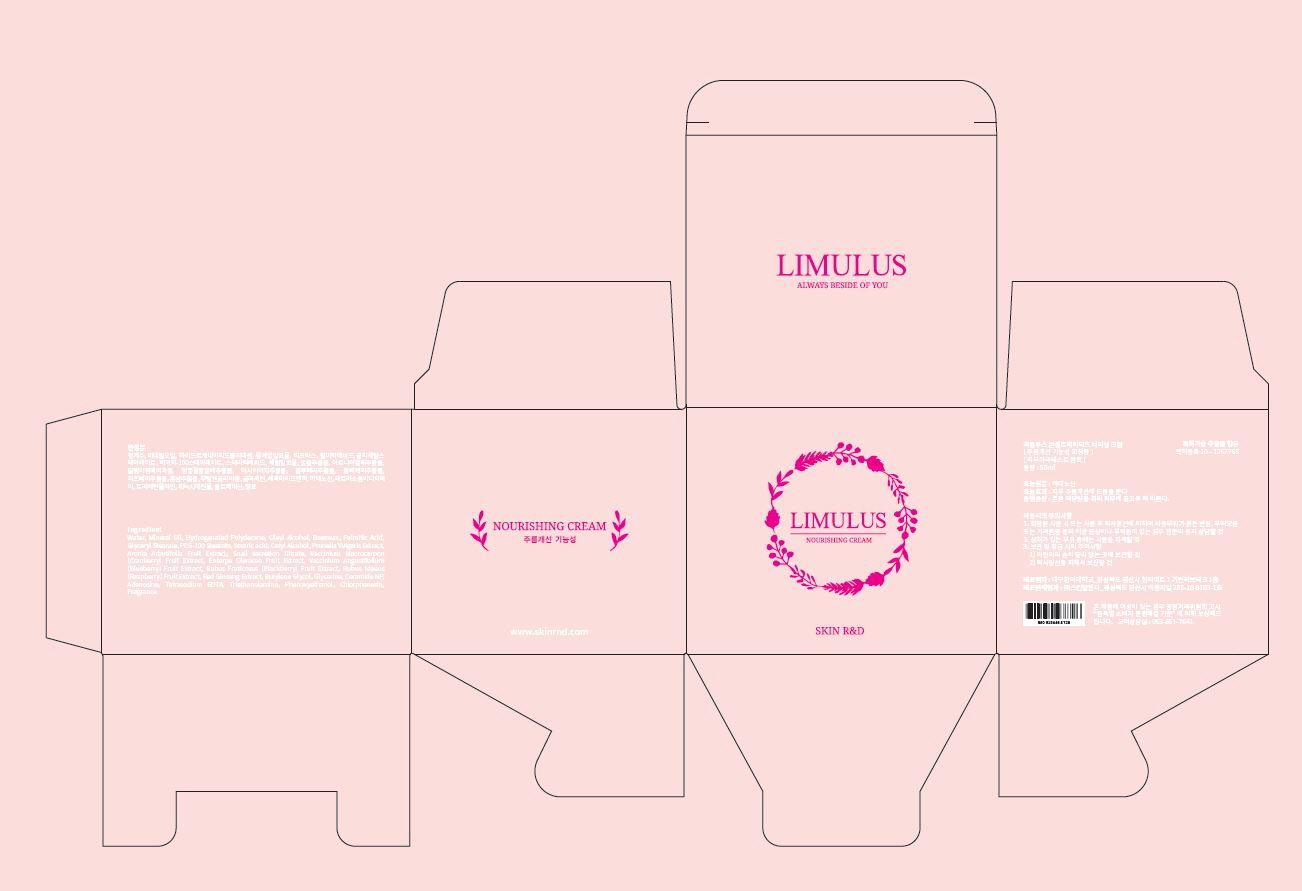 DRUG LABEL: Limulus Nourishing
NDC: 71464-0002 | Form: CREAM
Manufacturer: Skin R&D
Category: otc | Type: HUMAN OTC DRUG LABEL
Date: 20170703

ACTIVE INGREDIENTS: ADENOSINE 0.04 g/100 mL
INACTIVE INGREDIENTS: WATER; GLYCERIN

Drug Facts

ACTIVE INGREDIENT

Adenosine

INACTIVE INGREDIENT

Water
Mineral Oil
Hydrogenated Polydecene
Oleyl Alcohol
Stearic acid
Palmitic Acid
Glyceryl Stearate
PEG-100 Stearate
Beeswax
Cetyl Alcohol
Aronia Arbutifolia Fruit Extract
Glycerine
Butylene Glycol
Phenoxyethanol
Prunella Vulgaris Extract
Snail secretion filtrate
Phenoxyethanol
Vaccinium Macrocarpon (Cranberry) Fruit Extract
Euterpe Oleracea Fruit Extract
Vaccinium Angustifolium (Blueberry) Fruit Extract
Rubus Fruticosus (Blackberry) Fruit Extract
Rubus Idaeus (Raspberry) Fruit Extract
Triethanolamine
Phenoxyethanol
Fragrance
Chlorphenesin
Tetrasodium EDTA
Ceramide NP
Red Ginseng Extract

PURPOSE

Anti-wrinkle

keep out of reach of the children

INDICATIONS AND USAGE

Take an appropriate amount to the skin

WARNINGS

Precautions for Use

1. Consult with a medical specialist if any abnormal symptoms or side effects, such as red spots, swelling, or itching, occur during the use of this product.

2. Do not use the product on wounded areas.

3. Precautions for storage and handling

1) Keep out of reach of children.

2) Store away from direct sunlight.

DOSAGE AND ADMINISTRATION

for external use only